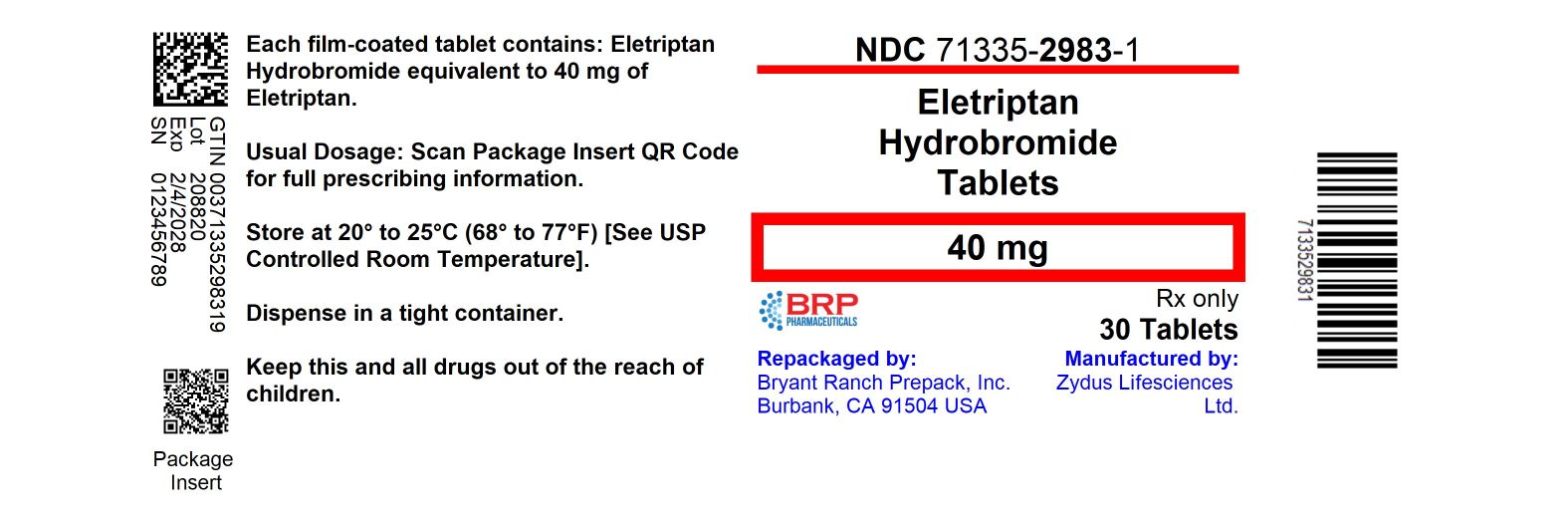 DRUG LABEL: Eletriptan hydrobromide
NDC: 71335-2983 | Form: TABLET, FILM COATED
Manufacturer: Bryant Ranch Prepack
Category: prescription | Type: HUMAN PRESCRIPTION DRUG LABEL
Date: 20260204

ACTIVE INGREDIENTS: ELETRIPTAN HYDROBROMIDE 40 mg/1 1
INACTIVE INGREDIENTS: ANHYDROUS LACTOSE; CROSCARMELLOSE SODIUM; FD&C YELLOW NO. 6; FERRIC OXIDE RED; FERRIC OXIDE YELLOW; HYPROMELLOSE, UNSPECIFIED; LACTOSE MONOHYDRATE; MAGNESIUM STEARATE; MICROCRYSTALLINE CELLULOSE 112; POVIDONE K30; TITANIUM DIOXIDE; TRIACETIN

ELETRIPTAN HYDROBROMIDE TABLETS

HOW SUPPLIED

Eletriptan Hydrobromide Tablets, 40 mg are brown colored, round shaped, biconvex with beveled edge, film-coated tablets, debossed with "923" on one side and plain on the other side and are supplied as follows:

- NDC 71335-2983-1: 30 Tablets in a BOTTLE

Store at 20° to 25°C (68° to 77°F) [See USP Controlled Room Temperature].

Dispense in a tight container.

Repackaged/Relabeled by:
Bryant Ranch Prepack
Burbank, CA 91504

PACKAGE LABEL

Eletriptan Hydrobromide 40mg Tablets